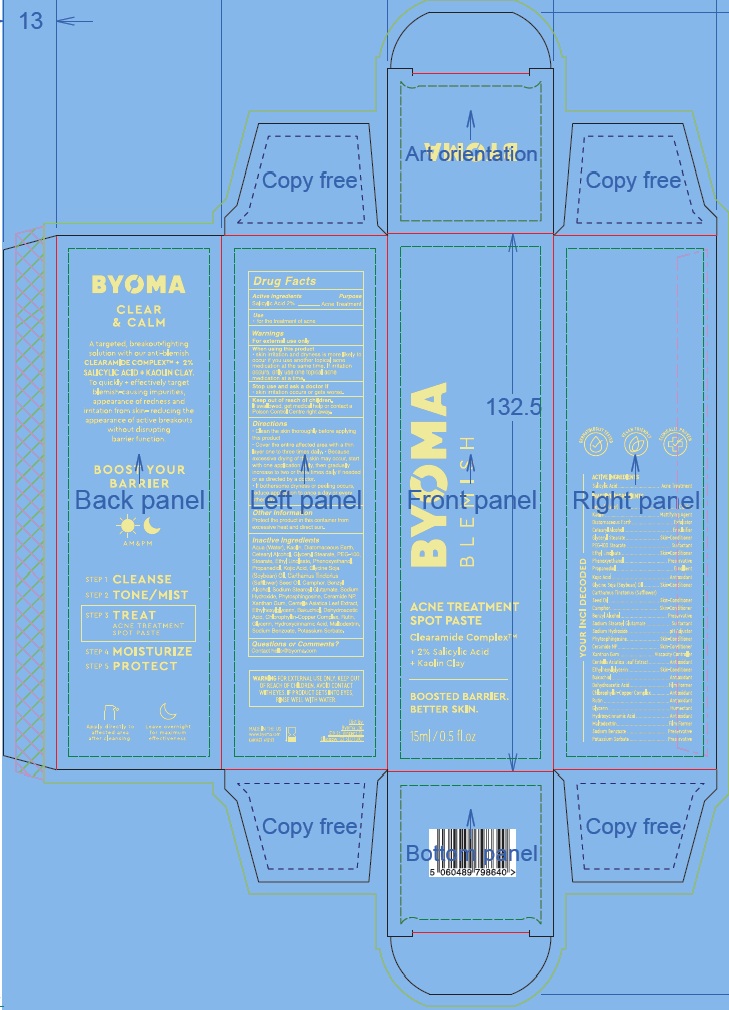 DRUG LABEL: Byoma Acne Treatment Spot
NDC: 84821-008 | Form: PASTE
Manufacturer: Byoma Ltd
Category: otc | Type: HUMAN OTC DRUG LABEL
Date: 20250423

ACTIVE INGREDIENTS: SALICYLIC ACID 20 mg/1 mL
INACTIVE INGREDIENTS: CENTELLA ASIATICA LEAF; SODIUM BENZOATE; DEHYDROACETIC ACID; SODIUM COPPER CHLOROPHYLLIN; HYDROXYCINNAMIC ACID; KAOLIN; ETHYL LINOLEATE; DIATOMACEOUS EARTH; GLYCERYL STEARATE; BAKUCHIOL; CERAMIDE NP; ETHYLHEXYLGLYCERIN; WATER; PHENOXYETHANOL; KOJIC ACID; PEG-100 STEARATE; PROPANEDIOL; SODIUM HYDROXIDE; CAMPHOR (NATURAL); RUTIN; BENZYL ALCOHOL; SODIUM STEAROYL GLUTAMATE; GLYCERIN; PHYTOSPHINGOSINE; CETEARYL ALCOHOL; SOYBEAN OIL; MALTODEXTRIN; SAFFLOWER OIL; POTASSIUM SORBATE; XANTHAN GUM

Byoma Acne Treatment Spot Paste

Active Ingredients

Salicylic Acid 2%

Purpose

Acne Treatment

Use

- for the treatment of acne

Warnings

For external use only

When using this product

- skin irritation and dryness is more likely to occur if you use another topical acne medication at the same time. If irritation occurs, only use one topical acne medication at a time.

Stop use and ask a doctor if

- skin irritation occurs or gets worse.

Keep out of reach of children.

If swallowed, get medical help or contact a Poison Control Centre right away.

Directions

- Clean the skin thoroughly before applying this product
- Cover the entire affected area with a thin layer one to three times daily.
- Because excessive drying of the skin may occur, start with one application daily, then gradually increase to two or three times daily if needed or as directed by a doctor.
- If bothersome dryness or peeling occurs, reduce application to once a day or every other day.

Other Information

Protect the product in this container from excessive heat and direct sun.

Inactive Ingredients

Aqua (Water), Kaolin, Diatomaceous Earth, Cetearyl Alcohol, Glyceryl Stearate, PEG-100 Stearate, Ethyl Linoleate, Phenoxyethanol, Propanediol, Kojic Acid, Glycine Soja (Soybean) Oil, Carthamus Tinctorius (Safflower) Seed Oil, Camphor, Benzyl Alcohol, Sodium Stearoyl Glutamate, Sodium Hydroxide, Phytosphingosine, Ceramide NP, Xanthan Gum, Centella Asiatica Leaf Extract, Ethylhexylglycerin, Bakuchiol, Dehydroacetic Acid, Chlorophyllin-Copper Complex, Rutin, Glycerin, Hydroxycinnamic Acid, Maltodextrin, Sodium Benzoate, Potassium Sorbate.

Questions or Comments?

Contact hello@byoma.com